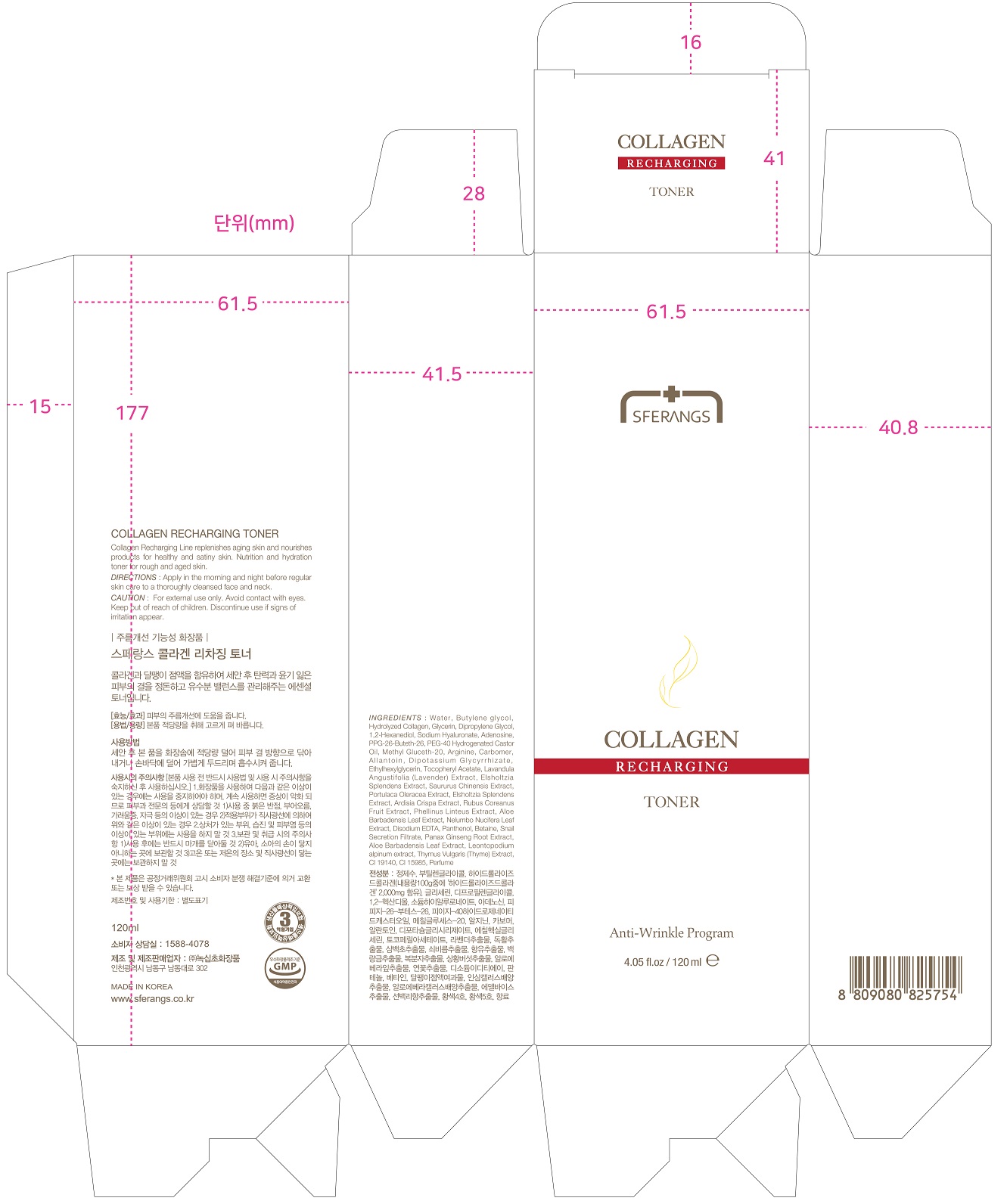 DRUG LABEL: SFERANGS COLLAGEN RECHARGING TONER
NDC: 73590-0039 | Form: LIQUID
Manufacturer: NOKSIBCHO cosmetic Co., Ltd.
Category: otc | Type: HUMAN OTC DRUG LABEL
Date: 20200430

ACTIVE INGREDIENTS: ADENOSINE 0.04 g/100 mL
INACTIVE INGREDIENTS: WATER

Drug Facts

ACTIVE INGREDIENT

adenosine

INACTIVE INGREDIENT

Water
Butylene glycol
Hydrolyzed Collagen
Glycerin
Dipropylene Glycol
1,2-Hexanediol
Sodium Hyaluronate
Phenoxyethanol
PPG-26-Buteth-26
PEG-40 Hydrogenated Castor Oil
Methyl Gluceth-20
Arginine
Carbomer
Allantoin
Dipotassium Glycyrrhizate
Ethylhexylglycerin
Tocopheryl Acetate
Propylene Glycol
Lavandula Angustifolia (Lavender) Extract
Saururus Chinensis Extract
Portulaca Oleracea Extract
Phellinus Linteus Extract
Aloe Barbadensis Leaf Extract
Nelumbo Nucifera Leaf Extract
Disodium EDTA
Panthenol
Betaine
Snail Secretion Filtrate
Panax ginseng culture extract
Caprylyl Glycol
Aloe vera Callus Culture Extract
Tropolone
Leontopodium alpinum extract
Thymus Vulgaris (Thyme) Extract
CI 19140
CI 15985
Parfum

PURPOSE

anti-wrinkle

keep out of reach of the children

INDICATIONS AND USAGE

apply proper amount to the skin

WARNINGS

For external use only
When using this product

■ if the following symptoms occurs after use, stop use and consult with a skin specialist

red specks, swelling, itching

■ don’t use on the part where there is injury, eczema, or dermatitis

Keep out of reach of children

■ if swallowed, get medical help or contact a person control center immediately